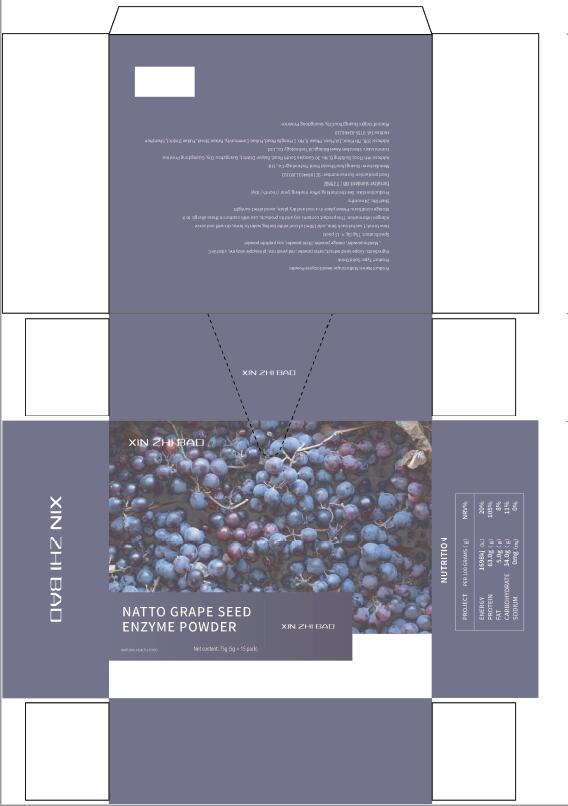 DRUG LABEL: NattoGrapeSeedEnzymePowder
NDC: 55030-002 | Form: POWDER
Manufacturer: Shenzhen Aiwei Biological Technology Co., Ltd.
Category: homeopathic | Type: HUMAN OTC DRUG LABEL
Date: 20200603

ACTIVE INGREDIENTS: ORANGE 0.25 g/5 g; MALTODEXTRIN 0.5 g/5 g; NATTOKINASE 0.25 g/5 g; RED YEAST 0.75 g/5 g; ASCORBIC ACID 0.35 g/5 g; STEM BROMELAIN 1.25 g/5 g; ARGININE 1 g/5 g; VITIS VINIFERA SEED 0.5 g/5 g
INACTIVE INGREDIENTS: SUCRALOSE; CITRIC ACID MONOHYDRATE; SILICON DIOXIDE

DOSAGE AND ADMINISTRATION

4g/bag, 1 bag a day

WARNINGS

Please keep out of the reach of children

INACTIVE INGREDIENT

Sucralose, citric acid, silica

INDICATIONS AND USAGE

: 2 times a day, 1-2 sachets each time, open the bag to eat or take it with warm water, or add it to juice and drinks

keep out of reach of children

PURPOSE

Replenish the protein needed by the body

ACTIVE INGREDIENT

Grape seed extract, natto powder, red yeast rice, pinea pple enzyme, vitaminC, Matcha powder, orange powder, litchi powder, soy p eptide powder